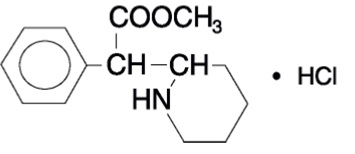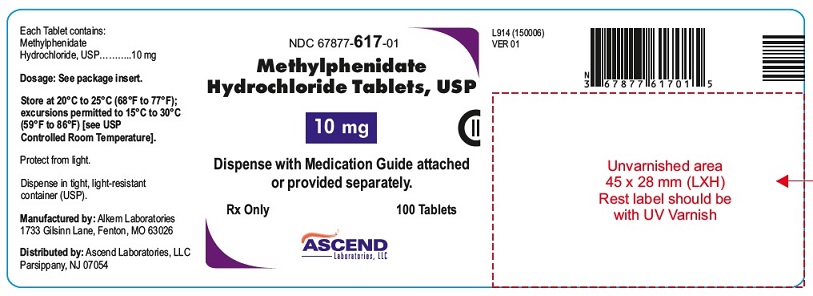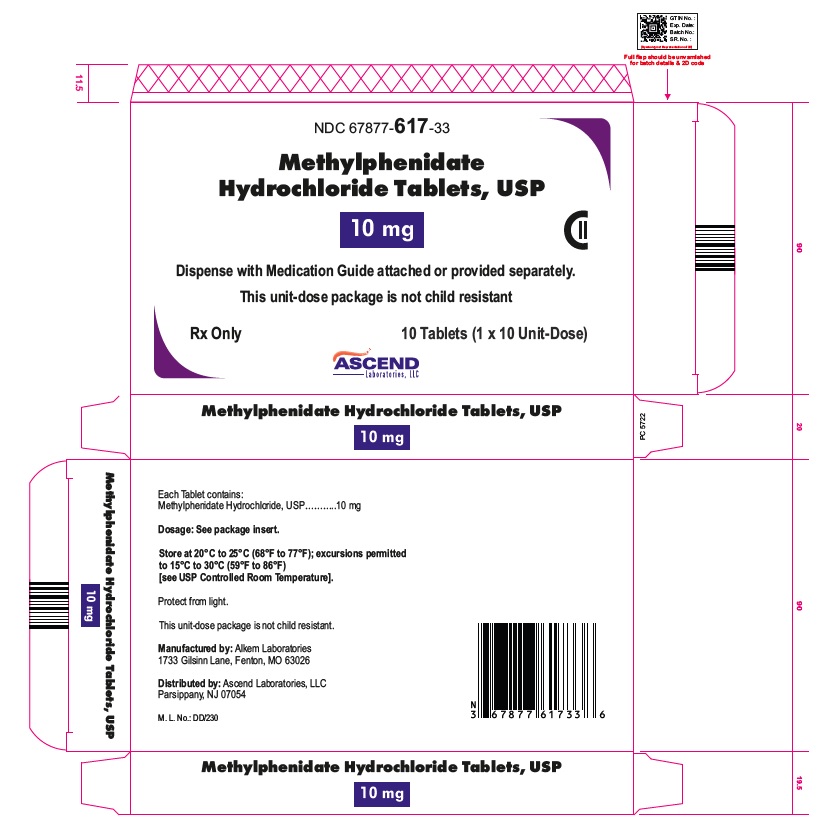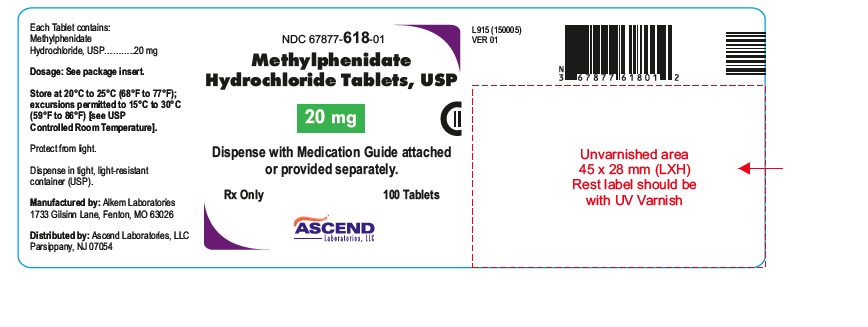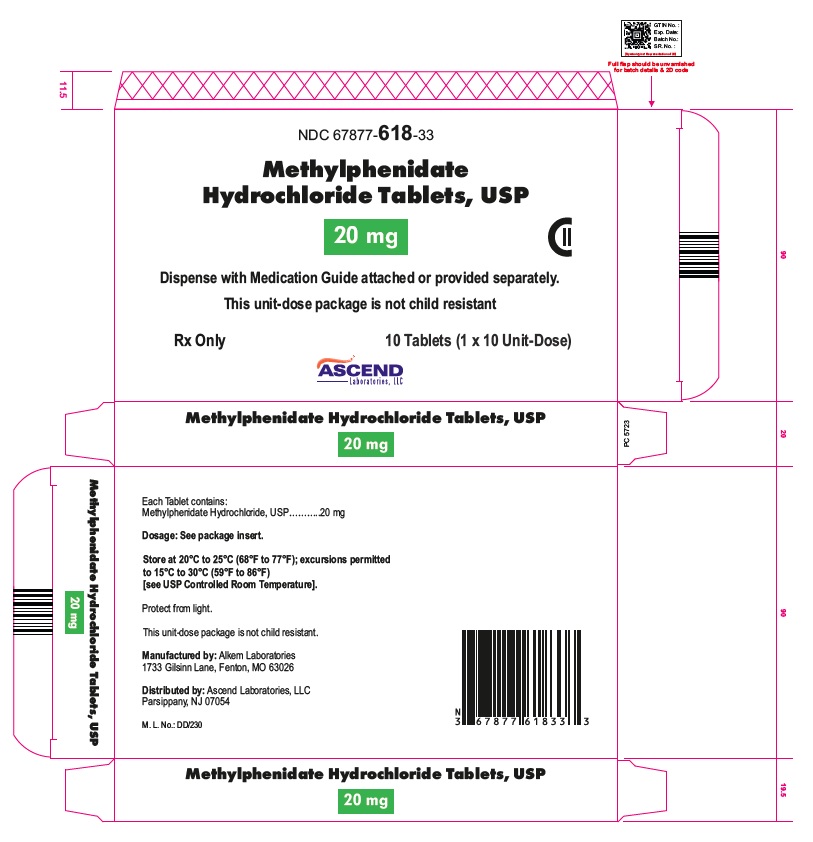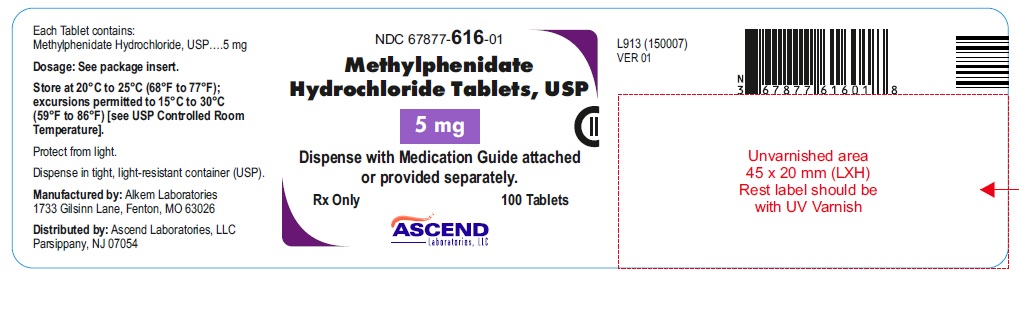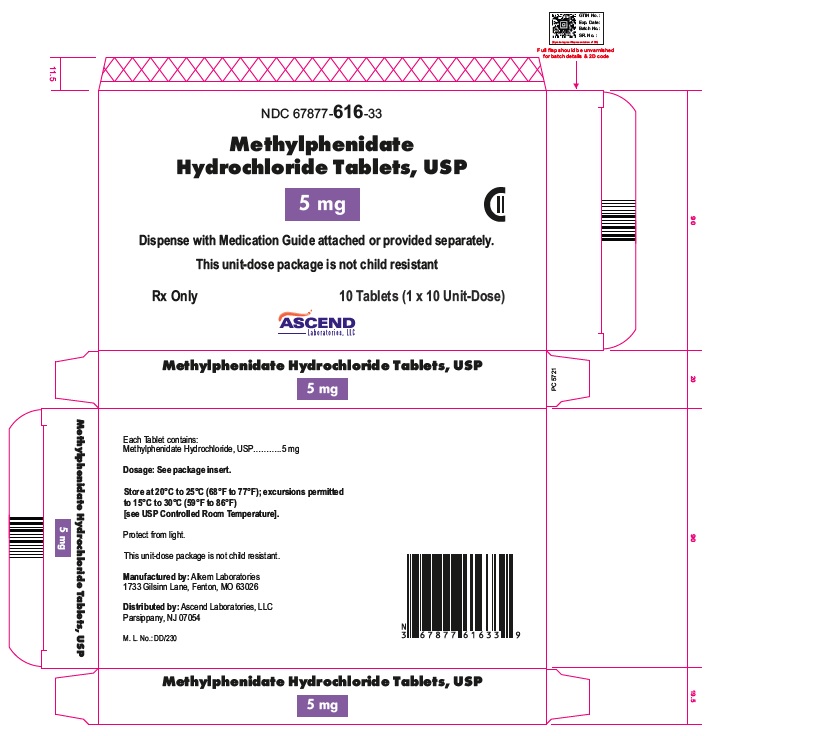 DRUG LABEL: Methylphenidate Hydrochloride
NDC: 67877-616 | Form: TABLET
Manufacturer: Ascend Laboratories, LLC
Category: prescription | Type: Human Prescription Drug Label
Date: 20240715
DEA Schedule: CII

ACTIVE INGREDIENTS: METHYLPHENIDATE HYDROCHLORIDE 5 mg/1 1
INACTIVE INGREDIENTS: LACTOSE MONOHYDRATE; SUCROSE; POLYETHYLENE GLYCOL, UNSPECIFIED; D&C YELLOW NO. 10; SILICON DIOXIDE; MAGNESIUM STEARATE; FD&C BLUE NO. 1; STARCH, CORN

HIGHLIGHTS OF PRESCRIBING INFORMATION

These highlights do not include all the information needed to use METHYLPHENIDATE HYDROCHLORIDE TABLETS safely and effectively. See full prescribing information for METHYLPHENIDATE HYDROCHLORIDE TABLETS.
METHYLPHENIDATE HYDROCHLORIDE tablets, for oral use, CII
Initial U.S. Approval: 1955

WARNING: ABUSE AND DEPENDENCE

See full prescribing informationforcomplete boxed warning.

- CNS stimulants, including methylphenidate hydrochloride tablets, other methylphenidate-containing products, and amphetamines, have a high potential for abuse and dependence (5.1,9.2,9.3).
- Assess the risk of abuse prior to prescribing, and monitor for signs of abuse and dependence while on therapy(5.1,9.2).

1 INDICATIONS AND USAGE

Methylphenidate hydrochloride is a centralnervoussystem(CNS) stimulant indicated for the treatment of Attention Deficit Hyperactivity Disorders(ADHD) and Narcolepsy(1).

2 DOSAGE AND ADMINISTRATION

Methylphenidate Hydrochloride Tablets (2.2):

- Pediatric Patients 6 Years and Older:Start with 5 mg twice daily (before breakfast and lunch), titrating the dose weekly in 5- to 10- mg increments. Dosages above 60 mg/dayare not recommended.
- Adults: Average daily dosage is 20 mg to 30 mg,administered 2 or 3 times daily,preferably 30 to 45 minutes before meals. Maximum total daily dosage is 60 mg.

3 DOSAGE FORMS & STRENGTHS

- Tablets: 5mg, 10mg, and 20 mg (3)

4 CONTRAINDICATIONS

- Known hypersensitivity to methylphenidate or other product components of methylphenidate hydrochloride tablets (4).
- Concurrent treatment with a monoamine oxidase inhibitor (MAOI), or use of an MAOI within the preceding 14 days (4).

5 WARNINGS AND PRECAUTIONS

- Serious CardiovascularEvents:Sudden death has been reported in association with CNS-stimulant treatment at usual doses in pediatric patients with structural cardiac abnormalities or other serious heart problems.In adults, sudden death, stroke, and myocardialinfarction have been reported. Avoid use in patients with known structuralcardiacabnormalities,cardiomyopathy, serious heart rhythm arrhythmias, or coronary artery disease (5.2).
- Blood Pressure and Heart RateIncreases:Monitorblood pressure and pulse. Consider the benefits and risk in patients for whom an increase in blood pressure or heartrate would be problematic(5.3).
- Psychiatric Adverse Reactions: Use of stimulantsmay cause psychotic or manicsymptoms in patients with no prior history or exacerbation of symptoms in patients with preexisting psychiatric illness. Evaluate for preexistingpsychotic or bipolar disorder prior to methylphenidate hydrochloride use(5.4).
- Priapism:Cases of painful and prolonged penile erections, and priapism have been reported with methylphenidateproducts.Immediatemedical attention should be sought if signs or symptoms of prolonged penile erections or priapism areobserved(5.5).
- Peripheral Vasculopathy, Including Raynaud’s Phenomenon:Stimulants used to treat ADHD are associated with peripheralvasculopathy,includingRaynaud’sphenomenon.Carefulobservation for digital changes is necessaryduringtreatment with ADHD stimulants(5.6).
- Long-Term Suppression of Growth: Monitor height and weight at appropriateintervals in pediatric patients (5.7).

6 ADVERSE REACTIONS

Commonadverse reactions: tachycardia, palpitations, headache, insomnia, anxiety, hyperhidrosis, weight loss, decreased appetite, dry mouth, nausea, and abdominal pain (6).
To report SUSPECTED ADVERSE REACTIONS, contact Ascend Laboratories, LLC at 1-877-ASC-RX01 (877-272-7901) or FDA at 1-800-FDA-1088 or www.fda.gov/medwatch.

7 DRUG INTERACTIONS

- Antihypertensive Drugs:Monitorbloodpressure.Adjust dosage of antihypertensive drug as needed (7.1).
- Halogenated Anesthetics: Avoid use of methylphenidate hydrochloride on the day of surgery if halogenated anesthetics will be used (7.1).

FULL PRESCRIBING INFORMATION

WARNING: ABUSE AND DEPENDENCE

CNSstimulants,including methylphenidate hydrochloride tablets, other methylphenidate-containing products, and amphetamines, have a highpotentialforabuseanddependence.Assesstherisk of abuse prior to prescribing, and monitor for signs of abuse and dependence while on therapy [see Warnings and Precautions (5.1), Drug Abuse and Dependence (9.2, 9.3)].

1 INDICATIONS AND USAGE

Methylphenidate hydrochloride tablets are indicated for the treatment of:

- Attention Deficit Hyperactivity Disorders (ADHD) in pediatric patients 6 years and older and adults
- Narcolepsy

2 DOSAGE AND ADMINISTRATION

2.1 Pretreatment Screening

Prior to treatingpediatricpatientsandadultswithcentral nervous system(CNS)stimulants,including methylphenidate hydrochloride tablets,assessforthepresenceofcardiacdisease(i.e.,perform a carefulhistory,includingfamilyhistory of suddendeathorventriculararrhythmia, and physicalexamination)[seeWarningsandPrecautions(5.2)].

Assesstheriskofabusepriortoprescribing,and monitorforsignsofabuseanddependencewhileontherapy.Maintaincarefulprescriptionrecords,educatepatientsaboutabuse,monitorforsigns of abuseandoverdose, and periodicallyreevaluate the needformethylphenidate hydrochloride tablets use[seeBoxedWarning,WarningsandPrecautions(5.1),DrugAbuseandDependence(9.2, 9.3)].

2.2 General Dosing Information

Methylphenidate Hydrochloride Tablets

Pediatric Patients 6 years and Older: Start with 5 mg orally twice daily (before breakfast and lunch). Increase dosage gradually, in increments of 5- to 10-mgweekly.Daily dosage above 60 mg is not recommended.

Adults: Average dosage is 20 to 30 mg daily. Administer orally in divided doses 2 or 3 times daily, preferably 30 to 45 minutes before meals. Maximum total daily dosage is 60 mg.Patients who are unable to sleep if medication is taken late in the dayshould take the last dose before 6 p.m.
Pharmacological treatment of ADHD may be needed for extended periods. Periodically reevaluate the long-term use of methylphenidate hydrochloride tablets, and adjust dosage as needed.

2.3 Dose Reduction and Discontinuation

If paradoxical worsening of symptoms or other adverse reactions occur, reduce the dosage,or, if necessary,discontinue methylphenidate hydrochloride tablets.Ifimprovement is notobservedafterappropriatedosageadjustmentover a one-monthperiod, the drugshouldbediscontinued.

3 DOSAGE FORMS & STRENGTHS

Tablets

- 5 mg, round, pale yellow to yellow uncoated tablet, debossed with "A62" on one side and plain on other side, may have mottled appearance.
- 10 mg, round, light blue to blue uncoated tablet, debossed with "A63" on one side and functionally scored on other side, may have mottled appearance.
- 20 mg, round, pale yellow to yellow uncoated tablet, debossed with "A64" on one side and functionally scored on other side, may have mottled appearance.

4 CONTRAINDICATIONS

- Hypersensitivity to methylphenidate or other components of methylphenidate hydrochloride tablets. Hypersensitivity reactions, such as angioedema and anaphylacticreactions, have been reported in patients treated with methylphenidate[seeAdverse Reactions (6.1)].
- Concomitant treatment with monoamine oxidase inhibitors (MAOIs), or within 14 daysfollowingdiscontinuation of treatment with an MAOI, because of the risk of hypertensive crises [see Drug Interactions (7.1)].

5 WARNINGS AND PRECAUTIONS

5.1 Potential for Abuse and Dependence

CNS stimulants,including methylphenidate hydrochloride tablets, other methylphenidate-containingproducts, and amphetamines, have a high potential for abuse and dependence. Assess the risk of abuse prior to prescribing, and monitor for signs of abuse and dependence while on therapy[seeBoxed Warning, Drug Abuse and Dependence (9.2, 9.3)].

5.2 Serious Cardiovascular Reactions

Sudden death, stroke, and myocardial infarction have been reported in adults with CNS stimulanttreatment at recommended doses. Sudden death has been reported in pediatric patients with structural cardiac abnormalities and other serious heart problems taking CNS stimulants at recommended doses for ADHD. Avoid use in patients with known serious structural cardiac abnormalities,cardiomyopathy, serious heart rhythm abnormalities,coronary artery disease, and other serious heart problems. Further evaluate patients who develop exertional chest pain, unexplained syncope, or arrhythmias during methylphenidate hydrochloride treatment.

5.3 Blood Pressure and Heart Rate Increases

CNS stimulants cause an increase in blood pressure (mean increaseapproximately 2 to 4 mmHg) and heart rate (mean increase approximately 3 to 6 beats per minute). Individuals may have larger increases. Monitor all patients for hypertension and tachycardia.

5.4 Psychiatric Adverse Reactions

Exacerbation of Preexisting Psychosis

CNS stimulants may exacerbate symptoms of behavior disturbance and thought disorder in patients with a preexisting psychoticdisorder.

Induction of a Manic Episode in Patients with Bipolar Disorder

CNS stimulants may induce a manic or mixedmood episode in patients. Prior to initiating treatment, screen patients for risk factors for developing a manic episode (e.g., comorbid or history of depressive symptoms or a family history of suicide, bipolar disorder, or depression).

New Psychotic or Manic Symptoms

CNS stimulants, at recommended doses, may cause psychotic or manic symptoms (e.g., hallucinations, delusional thinking, or mania) in patients without a prior history of psychotic illness or mania. If such symptoms occur, consider discontinuing methylphenidate hydrochloride. In a pooled analysis of multipleshort-term, placebo-controlled studies of CNS stimulants,psychotic or manicsymptoms occurred in approximately 0.1% of CNSstimulant-treated patients, compared to 0 in placebo-treated patients.

5.5 Priapism

Prolonged and painful erections, sometimes requiring surgical intervention, have been reported with methylphenidate products in both pediatric and adult patients. Priapism was not reported with drug initiation but developed after sometime on the drug, often subsequent to an increase in dose. Priapism has also appeared during a period of drug withdrawal (drug holidays or duringdiscontinuation).Patients who developabnormally sustained or frequent and painful erections should seek immediate medical attention.

5.6 Peripheral Vasculopathy, Including Raynaud’s Phenomenon

CNS stimulants, including methylphenidate hydrochloride, used to treat ADHD are associated with peripheral vasculopathy, including Raynaud’s phenomenon. Signs and symptoms are usuallyintermittent and mild; however, very rare sequelae include digital ulceration and/or soft tissue breakdown. Effects of peripheral vasculopathy, including Raynaud’s phenomenon, were observed in postmarketing reports at different times and at therapeutic doses in all age groups throughoutthe course of treatment. Signs and symptomsgenerallyimprove after reduction in dose or discontinuation of drug. Careful observation for digital changes is necessary during treatment with ADHD stimulants. Further clinical evaluation (e.g., rheumatology referral) may be appropriate for certain patients.

5.7 Long-Term Suppression of Growth

CNS stimulants have been associated with weight loss and slowing of growth rate in pediatric patients.

Careful follow-up of weight and height in pediatric patients ages 7 to 10 years who were randomized to either methylphenidate or non-medication treatment groups over 14 months, as well as in naturalistic subgroups of newly methylphenidate-treated and non-medication treated patients over 36 months (to the ages of 10 to 13 years), suggests that consistently medicated pediatric patients (i.e., treatment for 7 days per week throughoutthe year) have a temporary slowing in growth rate (on average, a total of about 2 cm less growth in height and 2.7 kg less growth in weight over 3 years), without evidence of growth reboundduringthis period of development.

Closely monitor growth (weight and height) in pediatric patients treated with CNS stimulants, including methylphenidate hydrochloride. Patients who are not growing or gainingheight or weight as expected may need to have their treatment interrupted.

6 ADVERSE REACTIONS

The following are discussed in more detail in other sections of the labeling:

- Abuse and Dependence [see Boxed Warning, Warningsand Precautions (5.1), Drug Abuse and Dependence (9.2, 9.3)]
- Knownhypersensitivity to methylphenidate or other ingredients of methylphenidate hydrochloride tablets [see Contraindications(4)]
- Hypertensive crisis with Concomitant Use of Monoamine Oxidase Inhibitors[seeContraindications (4), Drug Interactions (7.1)]
- Serious Cardiovascular Reactions [see Warningsand Precautions (5.2)]
- Blood Pressure and Heart Rate Increases [see Warnings and Precautions (5.3)]
- Psychiatric Adverse Reactions [seeWarningsandPrecautions(5.4)]
- Priapism [seeWarningsand Precautions (5.5)]
- Peripheral Vasculopathy, IncludingRaynaud’sPhenomenon[seeWarningsand Precautions (5.6)]
- Long-Term Suppression of Growth [see Warnings and Precautions (5.7)]

The following adverse reactions associated with the use of methylphenidate hydrochloride tablets, and othermethylphenidate products were identified in clinical trials,spontaneous reports, and literature. Because these reactions were reported voluntarily from a population of uncertain size, it is not always possible to estimate their frequency reliably or to establish a causal relationship to drug exposure.

Adverse Reactions Reported With methylphenidate hydrochloride

Infections andInfestations:nasopharyngitis

Blood and the Lymphatic System Disorders:leukopenia, thrombocytopenia,anemia

Immune System Disorders: hypersensitivity reactions, includingangioedema, and anaphylaxis

Metabolism and Nutrition Disorders: decreased appetite, reduced weight gain, and suppression of growth during prolongeduse in pediatric patients

Psychiatric Disorders: insomnia,anxiety, restlessness, agitation, psychosis(sometimes with visual and tactile hallucinations), depressed mood

Nervous System Disorders:headache, dizziness, tremor, dyskinesia, including choreoatheetoid movements, drowsiness, convulsions, cerebrovascular disorders (including vasculitis, cerebral hemorrhages and cerebrovascular accidents), serotonin syndrome in combination with serotonergic drugs

Eye Disorders: blurred vision, difficulties in visual accommodation

Cardiac Disorders: tachycardia,palpitations, increased blood pressure, arrhythmias, angina pectoris

Respiratory, Thoracic, and Mediastinal Disorders: cough

Gastrointestinal Disorders: dry mouth, nausea, vomiting,abdominal pain, dyspepsia

Hepatobiliary Disorders: abnormal liver function, ranging from transaminase elevation to severe hepatic injury

Skin andSubcutaneousTissue Disorders: hyperhidrosis, pruritus, urticaria, exfoliative dermatitis, scalp hair loss, erythemamultiforme rash, thrombocytopenic purpura

Musculoskeletal and Connective Tissue Disorders: arthralgia, muscle cramps, rhabdomyolysis

Investigations: weight loss (adult ADHD patients)

Additional Adverse Reactions Reported with Other Methylphenidate-ContainingProducts

The list below shows adverse reactions not listed for methylphenidate hydrochloride tablets that have been reported with other methylphenidate-containingproducts.

Blood and Lymphatic Disorders: pancytopenia

Immune System Disorders: hypersensitivity reactions, such as auricular swelling, bullous conditions, eruptions, exanthemas

Psychiatric Disorders: affect lability, mania,disorientation, and libido changes

Nervous System Disorders:migraine

Eye Disorders: diplopia, mydriasis

Cardiac Disorders: sudden cardiac death, myocardial infarction, bradycardia, extrasystole

Vascular Disorders: peripheral coldness, Raynaud'sphenomenon

Respiratory, Thoracic, and Mediastinal Disorders: pharyngolaryngeal pain, dyspnea

Gastrointestinal Disorders: diarrhea, constipation

Skin andSubcutaneousTissue Disorders: angioneuroticedema,erythema, fixed drug eruption

Musculoskeletal, Connective Tissue, and Bone Disorders: myalgia,muscle twitching

Renal and Urinary Disorders: hematuria

Reproductive System and Breast Disorders: gynecomastia

General Disorders: fatigue, hyperpyrexia

Urogenital Disorders: priapism

7 DRUG INTERACTIONS

7.1 Clinically Important Drug Interactions With methylphenidate hydrochloride

Table 1 presents clinically important drug interactions with methylphenidate hydrochloride.

Table 1: Clinically ImportantDrugInteractionswith methylphenidate hydrochloride

Monoamine Oxidase Inhibitors (MAOI)
Clinical Impact | Concomitant use of MAOIs and CNS stimulants, including methylphenidate hydrochloride can cause hypertensive crisis. Potential outcomes include death, stroke, myocardial infarction, aortic dissection, ophthalmological complications, eclampsia, pulmonary edema, and renal failure [see Contraindications (4)].
Intervention | Concomitant use of methylphenidate hydrochloride with MAOIs or within 14 days after discontinuing MAOI treatment is contraindicated.
Examples | selegiline, tranylcypromine, isocarboxazid, phenelzine, linezolid, methylene blue
Antihypertensive Drugs
Clinical Impact | Methylphenidate hydrochloride may decrease the effectiveness of drugs used to treat hypertension [see Warnings and Precautions(5.3)].
Intervention | Monitor blood pressure and adjust the dosage of the antihypertensive drug as needed.
Examples | Potassium-sparing and thiazide diuretics, calcium channel blockers, angiotensin-converting-enzyme (ACE) inhibitors, angiotensin II receptor blockers (ARBs), beta blockers, centrally acting alpha-2 receptor agonists
Halogenated Anesthetics
Clinical Impact | Concomitant use of halogenated anesthetics and methylphenidate hydrochloride may increase the risk of sudden blood pressure and heart rate increase during surgery.
Intervention | Avoid use of methylphenidate hydrochloride in patients being treated with anesthetics on the day of surgery.
Examples | halothane, isoflurane, enflurane, desflurane, sevoflurane

Risperidone
Clinical Impact | Combined use of methylphenidate with risperidone when there is a change, whether an increase or decrease, in dosage of either or both medications, may increase the risk of extrapyramidal symptoms (EPS)
Intervention | Monitor for signs of EPS

8 USE IN SPECIFIC POPULATIONS

8.1 Pregnancy

Pregnancy Exposure Registry

There is a pregnancy exposure registry that monitors pregnancy outcomes in women exposed to ADHD medications, including methylphenidate hydrochloride, during pregnancy. Healthcare providers are encouraged to register patients by calling the National Pregnancy Registry for ADHD Medications at 1-866-961-2388 or visit https://womensmentalhealth.org/adhd-medications/.

Risk Summary

Published studies and postmarketing reports on methylphenidate use during pregnancy have not identified a drug-associated risk of major birth defects, miscarriage or adverse maternal or fetal outcomes. There may be risks to the fetus associated with the use of CNS stimulants use during pregnancy (see Clinical Considerations).

No effects on morphological development were observed in embryo-fetal development studies with oral administration of methylphenidate to pregnant rats and rabbits during organogenesis at doses up to 10 and 15 times, respectively, the maximum recommended human dose (MRHD) of 60 mg/day given to adolescents on a mg/m^2 basis. However, spina bifida was observed in rabbits at a dose 52 times the MRHD given to adolescents. A decrease in pup body weight was observed in a pre- and post-natal development study with oral administration of methylphenidate to rats throughout pregnancy and lactation at doses 6 times the MRHD given to adolescents (see Data).

The estimated background risk of major birth defects and miscarriage for the indicated population is unknown. All pregnancies have a background risk of birth defect, loss, or other adverse outcomes. In the U.S. general population, the estimated background risk of major birth defects and miscarriage in clinically recognized pregnancies is 2% to 4% and 15% to 20%, respectively.

Clinical Considerations

Fetal/Neonatal Adverse Reactions

CNS stimulants, such as methylphenidate hydrochloride, can cause vasoconstriction and thereby decrease placental perfusion. No fetal and/or neonatal adverse reactions have been reported with the use of therapeutic doses of methylphenidate during pregnancy; however, premature delivery and low birth weight infants have been reported in amphetamine-dependent mothers.

Data

Animal Data

In embryo-fetal development studies conducted in rats and rabbits, methylphenidate was administered orally at doses of up to 75 and 200 mg/kg/day, respectively, during the period of organogenesis. Malformations (increased incidence of fetal spina bifida) were observed in rabbits at the highest dose, which is approximately 52 times the MRHD of 60 mg/day given to adolescents on a mg/m^2 basis. The no effect level for embryo-fetal development in rabbits was 60 mg/kg/day (15times the MRHD given to adolescents on a mg/m^2 basis). There was no evidence of morphological development effects in rats, although increased incidences of fetal skeletal variations were seen at the highest dose level (10 times the MRHD of 60 mg/day given to adolescents on a mg/m^2 basis), which was also maternally toxic. The no effect level for embryo-fetal development in rats was 25 mg/kg/day (3 times the MRHD on a mg/m^2 basis). When methylphenidate was administered to rats throughout pregnancy and lactation at doses of up to 45 mg/kg/day, offspring body weight gain was decreased at the highest dose (6 times the MRHD of 60 mg/day given to adolescents on a mg/m^2 basis), but no other effects on postnatal development were observed. The no effect level for pre- and postnatal development in rats was 15 mg/kg/day (~2 times the MRHD given to adolescents on a mg/m^2 basis).

8.2 Lactation

Risk Summary

Limited published literature, based on milk sampling from seven mothers reports that methylphenidate is present in human milk, which resulted in infant doses of 0.16% to 0.7% of the maternal weight-adjusted dosage and a milk/plasma ratio ranging between 1.1 and 2.7. There are no reports of adverse effects on the breastfed infant and no effects on milk production. Long-term neurodevelopmental effects on infants from stimulant exposure are unknown. The developmental and health benefits of breastfeeding should be considered along with the mother’s clinical need for methylphenidate hydrochloride and any potential adverse effects on the breastfed infant from methylphenidate hydrochloride or from the underlying maternal condition.

Clinical Considerations

Monitor breastfeeding infants for adverse reactions, such as agitation, insomnia, anorexia, and reduced weight gain.

8.4 Pediatric Use

The safety and effectiveness of methylphenidate hydrochloride for the treatment of ADHD have been established in pediatric patients 6 to 17 years.

The safety and effectiveness of methylphenidate hydrochloride in pediatric patients less than 6 years have not been established.

The long-term efficacy of methylphenidate hydrochloride in pediatric patients has not been established.

Long-Term Suppression of Growth

Growth should be monitored during treatment with stimulants, including methylphenidate hydrochloride. Pediatric patients who are not growing or gaining weight as expected may need to have their treatment interrupted [see Warnings and Precautions (5.7)].

Juvenile Animal Toxicity Data

Rats treated with methylphenidate early in the postnatal period through sexual maturation demonstrated a decrease in spontaneous locomotor activity in adulthood. A deficit in acquisition of a specific learning task was observed in females only. The doses at which these findings were observed are at least 4 times the MRHD of 60 mg/day given to children on a mg/m^2 basis.

In a study conducted in young rats, methylphenidate was administered orally at doses of up to 100 mg/kg/day for 9 weeks, starting early in the postnatal period (postnatal Day 7) and continuing through sexual maturity (postnatal Week 10). When these animals were tested as adults (postnatal Weeks 13 to 14), decreased spontaneous locomotor activity was observed in males and females previously treated with 50 mg/kg/day (approximately 4 times the MRHD of 60 mg/day given to children on a mg/m^2 basis) or greater, and a deficit in the acquisition of a specific learning task was seen in females exposed to the highest dose (8 times the MRHD given to children on a mg/m^2 basis). The no effect level for juvenile neurobehavioral development in rats was 5 mg/kg/day (approximately 0.5 times the MRHD given to children on a mg/m^2 basis). The clinical significance of the long-term behavioral effects observed in rats is unknown.

8.5 Geriatric Use

Methylphenidate hydrochloride has not been studied in the geriatricpopulation.

9 DRUG ABUSE AND DEPENDENCE

9.1 Controlled Substance

Methylphenidate hydrochloride tablets contain methylphenidate hydrochloride, a Schedule II controlledsubstance.

9.2 Abuse

CNS stimulants,including methylphenidate hydrochloride, have a high potential for abuse. Abuse is characterized by impaired control over drug use despiteharm, and craving.

Signs and symptoms of CNS stimulant abuse include increased heart rate, respiratory rate, blood pressure, and/or sweating, dilated pupils, hyperactivity, restlessness,insomnia, decreased appetite, loss of coordination, tremors, flushed skin, vomiting, and/or abdominal pain. Anxiety,psychosis, hostility, aggression, and suicidal or homicidal ideation have also been observed. Abusers of CNS stimulantsmay chew, snort, inject, or use other unapproved routes of administration which may result in overdose and death [see Overdosage (10)].

To reduce the abuse of CNS stimulants, including methylphenidate hydrochloride, assess the risk of abuse prior to prescribing. After prescribing, keep careful prescription records, educate patients and their families about abuse and on proper storage and disposal of CNS stimulants[see How Supplied/Storage and Handling (16)], monitor for signs of abuse while on therapy, and reevaluate the need for methylphenidate hydrochloride use.

9.3 Dependence

Tolerance

Tolerance (a state of adaptation in which exposure to a drug results in a reduction of the drug's desired and/or undesired effects over time) can occur during chronic therapy with CNS stimulants, including methylphenidate hydrochloride.

Dependence

Physical dependence (which is manifested by a withdrawal syndrome produced by abrupt cessation, rapid dose reduction, or administration of an antagonist)may occur in patients treated with CNS stimulants, including methylphenidate hydrochloride. Withdrawal symptoms after abrupt cessation following prolonged high-dosage administration of CNS stimulants include dysphoric mood; fatigue; vivid, unpleasant dreams; insomnia or hypersomnia; increased appetite; and psychomotor retardation or agitation.

10 OVERDOSAGE

Human Experience
Signs and symptoms of acute overdosage, resulting principally from overstimulation of the central nervous system and from excessive sympathomimetic effects, may include the following: nausea, vomiting, diarrhea, restlessness, anxiety, agitation, tremors, hyperreflexia, muscle twitching, convulsions (which may be followed by coma), euphoria, confusion, hallucinations, delirium, sweating, flushing, headache, hyperpyrexia, tachycardia, palpitations, cardiac arrhythmias, hypertension, hypotension, tachypnea, mydriasis, dryness of mucous membranes, and rhabdomyolysis.
Overdose Management
Consult with a Certified Poison Control Center (1-800-222-1222) for the latest recommendations.

11 DESCRIPTION

Methylphenidate hydrochloride tablets USP contains methylphenidate hydrochloride, a CNS stimulant. It is available as tablets of 5mg, 10mg, and 20 mg strength for oral administration.
Methylphenidate hydrochloride is methyl α-phenyl-2-piperidineacetate hydrochloride, and its structural formula is:

Methylphenidate hydrochloride USP is a white, odorless, fine crystalline powder. Its solutions are acid to litmus. It is freely soluble in water and in methanol, soluble in alcohol, and slightly soluble in chloroform and in acetone. Its molecular weight is 269.77 g/mol.
Methylphenidate hydrochloride tablets USP contains the following inactive ingredients: Colloidal Silicon Dioxide, D&C Yellow #10 Aluminium lake, FD&C Blue #1/Brilliant Blue FCF Aluminium lake (10-mg tablets), Lactose Monohydrate, Magnesium Stearate, Polyethylene glycol, Pregelatinized starch (5-mg and 20-mg tablets), Sucrose.

12 CLINICAL PHARMACOLOGY

12.1 Mechanism of Action

Methylphenidatehydrochloride is a CNS stimulant. The mode of therapeutic action in ADHD and narcolepsy is not known.

12.2 Pharmacodynamics

Methylphenidate is a racemic mixturecomprised of the d- and l-threo enantiomers. The d-threo enantiomer is more pharmacologically active than the l-threo enantiomer.Methylphenidateblocksthe reuptake of norepinephrine and dopamine into the presynaptic neuron and increase the release of these monoamines into the extraneuronal space.

Cardiac Electrophysiology

A formal QT study has not been conducted in patients taking methylphenidate.

The effect of dexmethylphenidate, the pharmacologically active d-enantiomer of methylphenidate, on the QT interval was evaluated in a double-blind, placebo- and open-label active(moxifloxacin)-controlled study following single doses of dexmethlyphenidate XR 40 mg(maximum recommended adult total daily dosage) in 75 healthyvolunteers.

Electrocardiograms were collected up to 12 hourspostdose. Frederica’s method for heart rate correction was employed to derive the corrected QT interval (QTcF). The maximum mean prolongation of QTcF intervals was less than 5 ms, and the upperlimit of the 90% confidence interval was below 10 ms for all time-matchedcomparisons versus placebo. This was below the threshold of clinical concern and there was no evident exposure response relationship.

12.3 Pharmacokinetics

Absorption

Methylphenidate in the extended-release tablets is more slowly but as extensively absorbed as in the regular tablets. Relative bioavailability of the extended-release tablet compared to the methylphenidate hydrochloride tablet, measured by the urinary excretion of methylphenidate major metabolite (α-phenyl-2-piperidine acetic acid) was 105% (49% to 168%) in children and 101% (85% to 152%) in adults. The time to peak rate in children was 1.9 hours (0.3 to 4.4 hours) for the methylphenidate hydrochloride tablets and 4.7 hours(1.3 to 8.2hours) for the methylphenidate hydrochloride extended-release tablets. An average of 67% of extended-release tablet dose was excreted in children as compared to 86% in adults.

Effect of Food

After a high-fat meal, both area under the curve (AUC) (by 25 %) and Cmax (by 27 %) are higher. Time to Cmax (Tmax) is faster after a high-fat meal (median Tmax: 2.5 hours) ascompared to without food (median Tmax: 3 hours).

Distribution

Binding toplasma proteins is low (10% to 33%). The volume of distribution was 2.65 ± 1.11L/kg for d-methylphenidate and 1.80 ± 0.91L/kg for l- methylphenidate.

Elimination

The systemic clearance is 0.40 ± 0.12 L/h/kg for d-methylphenidate and 0.73 ± 0.28L/h/kg for l-methylphenidate.

Metabolism

Methylphenidate is metabolizedprimarily by de-esterification to alpha-phenyl-piperidine acetic acid (ritalinic acid), which has little or no pharmacologic activity.

Excretion

After oral administration, 78% to 97% of the dose is excreted in the urine and 1% to 3% in feces in the form of metabolites within 48 to 96 hours. Most of the dose is excreted in the urine as alpha-phenyl-2-piperidine acetic acid (60% to 86%). The cumulative urinary excretion of alpha-phenyl-2-piperidine acetic acid are not significantly different for methylphenidate hydrochloride extended-release tablets.

Studies in SpecificPopulations

Male and Female Patients

In a clinical study involving adult subjects who received methylphenidate hydrochloride extended-release tablets, plasma concentrations of methylphenidate’s major metabolite appeared to be greater in females than in males. No gender differences were observed for methylphenidate plasma concentration in the same subjects.

Racial or Ethnic Groups

There is insufficient experience with the use ofmethylphenidate to detectethnic variations in pharmacokinetics.

Patients with Renal Impairment

Methylphenidate has not been studied in renally-impaired patients. Renal impairment is expected to have minimal effect on the pharmacokinetics of methylphenidate since less than 1% of a radiolabeled dose is excreted in the urine as unchanged compound,and the major metabolite (ritalinic acid), has little or no pharmacologic activity.

Patients with Hepatic Impairment

Methylphenidate has not been studied in patients with hepatic impairment.Hepaticimpairment is expected to have minimal effect on the pharmacokinetics of methylphenidate since it is metabolizedprimarily to ritalinic acid by nonmicrosomalhydrolytic esterases that are widely distributedthroughoutthebody.

13 NONCLINICAL TOXICOLOGY

13.1 Carcinogenesis, Mutagenesis, and Impairment of Fertility

Carcinogenesis

In a lifetime carcinogenicity study carriedout in B6C3F1mice, methylphenidate caused an increase in hepatocellular adenomas, and in males only, an increase in hepatoblastomas at a daily dose of approximately 60 mg/kg/day.Thisdose is approximately 2 times the MRHD of 60mg/day given to children on mg/m2 basis.

Hepatoblastoma is a relatively rare rodentmalignanttumor type. There was no increase in totalmalignant hepatic tumors.Themouse strain used is sensitive to the development of hepatictumors and thesignificance of these results tohumansis unknown.

Methylphenidatedidnotcause any increase in tumors in a lifetimecarcinogenicity study carriedout in F344 rats; the highest dose used wasapproximately 45 mg/kg/day,which is approximately 4 times the MRHD (children) on a mg/m2 basis.

In a 24-week carcinogenicity study in the transgenic mouse strain p53+/-, which is sensitive to genotoxic carcinogens, there was no evidence of carcinogenicity. Male and femalemice were fed diets containing the same concentration of methylphenidate as in the lifetime carcinogenicity study; the high-dose groups were exposed to 60 to 74mg/kg/day of methylphenidate.

Mutagenesis

Methylphenidate was not mutagenic in the in vitro Ames reverse mutation assay, in the in vitromouse lymphoma cell forward mutation assay, or in the in vitro chromosomal aberration assay using human lymphocytes. Sister chromatid exchanges and chromosome aberrations were increased, indicative of a weak clastogenic response, in an in vitro assay in cultured Chinese Hamster Ovary cells. Methylphenidate was negative invivo in males and females in the mouse bone marrow micronucleus assay.

ImpairmentofFertility

No human data on the effect of methylphenidate on fertility are available. Methylphenidate did not impair fertility in male or female mice that were fed diets containing the drug in an 18-week continuous breeding study. The study was conducted at doses up to 160 mg/kg/day,approximately 10 times the MRHD of 60mg/day given to adolescents on a mg/m2 basis.

16 HOW SUPPLIED/STORAGE AND HANDLING

Methylphenidate Hydrochloride Tablets, USP

- 5 mg tablets: Round, pale yellow to yellow uncoated tablet, debossed with "A62" on one side and plain on other side, may have mottled appearance.

NDC 67877-616-01

Bottles of 100 Tablets

NDC 67877-616-33

Carton of 10 Tablets (1 X 10 Unit-Dose)

- 10 mg tablets: Round, light blue to blue uncoated tablet, debossed with "A63" on one side and functionally scored on other side, may have mottled appearance.

NDC 67877-617-01

Bottles of 100 Tablets

NDC 67877-617-33

Carton of 10 Tablets (1 X 10 Unit-Dose)

- 20 mg tablets: Round, pale yellow to yellow uncoated tablet, debossed with "A64" on one side and functionally scored on other side, may have mottled appearance.

NDC 67877-618-01

Bottles of 100 Tablets

NDC 67877-618-33

Carton of 10 Tablets (1 X 10 Unit-Dose)
Store at 20°C to 25°C (68°F to 77°F); excursions permitted to 15°C to 30°C (59°F to 86°F) [see USP controlled room temperature]. Protect from light.

Dispense in tight, light-resistant container (USP).

Disposal

Comply with local laws and regulations on drugdisposal of CNS stimulants. Dispose of remaining, unused, or expired methylphenidate hydrochloride tabletsby a medicine takeback program or by an authorized collector registered with the Drug EnforcementAdministration. If no take-back program or authorized collector is available, mix methylphenidate hydrochloride tablets with an undesirable, nontoxic substance to make it less appealing to children and pets. Place the mixture in a container, such as a sealed plastic bag and discard methylphenidate hydrochloride tablets in the householdtrash.

17 PATIENT COUNSELING INFORMATION

Advise the patient to read the FDA-approved patient labeling (Medication Guide).

Controlled Substance Status/High Potential for Abuse and Dependence

Advise patients that methylphenidate hydrochloride tablets are controlled substances, and they can be abused and lead to dependence. Instruct patients that theyshould not give methylphenidate hydrochloride tablets to anyone else. Advise patients to store methylphenidate hydrochloride tablets in a safe place, preferably locked, to prevent abuse. Advise patients to comply with laws and regulations on drug disposal. Advise patients to dispose of remaining, unused, or expired methylphenidate hydrochloride tablets by a medicine take-back program if available [see Boxed Warning, Warnings and Precautions (5.1), Drug Abuse and Dependence (9.1, 9.2, 9.3), How Supplied/Storage and Handling(16)].

Serious Cardiovascular Risks

Advise patients that there is a potential serious cardiovascular risk, including sudden death, myocardial infarction, stroke, and hypertension with methylphenidate hydrochloride tablets use. Instruct patients to contact a healthcare provider immediately if they develop symptoms, such as exertional chest pain, unexplained syncope, or other symptoms suggestive of cardiac disease [see Warnings and Precautions (5.2)].

Blood Pressure and Heart Rate Increases

Instruct patients that methylphenidate hydrochloride tablets can cause elevations of their blood pressure and pulse rate [see Warnings and Precautions (5.3)].

Psychiatric Risks

Advise patients that methylphenidate hydrochloride tablets, at recommended doses, can cause psychotic or manic symptoms, even in patients without prior history of psychotic symptoms or mania[see Warnings and Precautions (5.4)].

Priapism

Advise patients of the possibility of painful or prolonged penile erections (priapism). Instruct them to seek immediate medical attention in the event of priapism[see Warnings and Precautions (5.5)].

Circulation Problems in Fingers and Toes [Peripheral Vasculopathy, Including Raynaud’s Phenomenon]

Instruct patients about the risk of peripheral vasculopathy, including Raynaud’s phenomenon, and associated signs and symptoms: fingers or toes may feel numb, cool, painful,and/or may change color from pale, to blue, to red. Instruct patients to report to their physician any new numbness, pain, skin color change, or sensitivity to temperature in fingers or toes.

Instruct patients to call their physician immediately with any signs of unexplained wounds appearing on fingers or toes while taking methylphenidate hydrochloride tablets. Further clinical evaluation (e.g., rheumatology referral) may be appropriate for certain patients [see Warnings and Precautions (5.6)].

Suppression of Growth

Advise patients that methylphenidate hydrochloride tablets may cause slowing of growth and weight loss [see Warnings and Precautions (5.7)].

Pregnancy Registry

Advise patients that there is a pregnancy exposure registry that monitors pregnancy outcomes in patients exposed to ADHD medications, including methylphenidate hydrochloride tablets , during pregnancy [see Use in Specific Populations (8.1)].

Manufactured by:

Alkem Laboratories

1733 Gilsinn Lane, Fenton, MO 63026

Distributed by:

Ascend Laboratories, LLC

Parsippany, NJ 07054

MEDICATION GUIDE

Methylphenidate Hydrochloride Tablets, USP CII

[(meth′′ il fen′ i date hye′′ droe klor′ ide)]

Whatis themost important information I should knowabout methylphenidate hydrochloride tablets?

Methylphenidate hydrochloride tablets is a federal controlled substance (CII) because it canbe abused or lead to dependence.Keep methylphenidate hydrochloride tablets in a safe place to prevent misuse and abuse. Selling or giving away methylphenidate hydrochloride tablets may harm others and is against the law.

Tell your doctor if you or your child have abused orbeendependent on alcohol, prescription medicines, or street drugs.

The following have beenreported with use of methylphenidate hydrochloride and other stimulantmedicines:

1. Heart-related problems:

- sudden death in patients who have heart problems or heart defects
- stroke and heart attack in adults
- increased blood pressure and heart rate

Tell your doctor if you or your child haveany heart problems,heartdefects, highblood pressure, or a family history of theseproblems.

Your doctor should check you or yourchild carefully for heart problems before starting methylphenidate hydrochloride tablets.

Your doctor should check you or your child’s blood pressureand heart rateregularly during treatment with methylphenidate hydrochloride tablets.

Call your doctor right away if you or your child has any signs of heart problems, such as chest pain, shortness of breath, or fainting while taking methylphenidate hydrochloride tablets.

2. Mental (psychiatric) problems:

All Patients

- new or worse behavior and thought problems
- new or worse bipolar illness
- new or worse aggressivebehavior orhostility
- new psychotic symptoms (such as hearing voices, believing things thatarenot true, aresuspicious)or newmanic symptoms

Tell your doctor about any mental problems you or your child have, or about a family history of suicide, bipolar illness, ordepression.

Callyour doctor right awayifyou oryour child have any neworworsening mental symptoms or problemswhile taking methylphenidate hydrochloride tablets, especially seeing or hearing things thatare not real, believing things that are not real, or aresuspicious.

What is methylphenidate hydrochloride tablets?

- Methylphenidate hydrochloride tablets is a central nervous system (CNS) stimulant prescription medicine. It is used for the treatment of Attention DeficitHyperactivityDisorder (ADHD).Methylphenidate hydrochloride tablets may help increase attention and decreaseimpulsiveness and hyperactivity in patientswith ADHD.
- Methylphenidate hydrochloride tablets should be used as a part of a total treatment program for ADHD that may include counseling or other therapies.
- Methylphenidate hydrochloride tablets is also used in the treatment of a sleep disordercalled narcolepsy.

It is not known if methylphenidate hydrochloride tablets is safe and effective inchildren under 6 yearsof age.

Who should not take methylphenidate hydrochloride tablets?

Methylphenidate hydrochloride tablets should not be taken if you or your child:

- are allergictomethylphenidate hydrochloride, orany of theingredients in methylphenidate hydrochloride tablets. See the end of this Medication Guide for a complete list of ingredients in methylphenidate hydrochloride tablets.
- are taking or have taken within the past 14 days an anti-depression medicine called a monoamine oxidase inhibitor (MAOI).

Methylphenidate hydrochloride tablets may not be right foryou oryour child. Before starting methylphenidate hydrochloride tablets, tell your oryourchild’s doctor about all health conditions (or a family history of), including:

- heart problems, heart defects, high blood pressure
- mental problems, including psychosis, mania, bipolarillness, or depression
- circulation problems in fingers or toes
- if you are pregnant or plan to becomepregnant. It is not known if methylphenidate hydrochloride tablets will harm your unborn baby.

o There is a pregnancy registry for females who are exposed to ADHD medications, including methylphenidate hydrochloride tablets, during pregnancy. The purpose of the registry is to collect information about the health of females exposed to methylphenidate hydrochloride tablets and their baby. If you or your child becomes pregnant during treatment with methylphenidate hydrochloride tablets, talk to your healthcare provider about registering with the National Pregnancy Registry of ADHD Medications at 1-866-961-2388 or visit online at https://womensmentalhealth.org/adhd-medications/.

- if you are breastfeedingor plan to breastfeed.Methylphenidate passesintoyourbreastmilk. Talk to your healthcare provider about the best way to feed your baby during treatment with methylphenidate hydrochloride tablets.

Tell your doctor about all of the medicines thatyou or your child takes, including prescription and over-the-countermedicines, vitamins, and herbal supplements. Methylphenidate hydrochloride tablets and some medicines may interact with each other and causeserious side effects. Sometimes the doses of other medicines will need to be adjusted while taking methylphenidate hydrochloride tablets.

Your doctorwill decide whethermethylphenidate hydrochloride tablets can be taken with other medicines.

Especially tell your doctor ifyou oryour child takes:

- anti-depression medicines, including MAOIs
- blood pressure medicines (anti-hypertensive)

Know the medicines that you or yourchild takes. Keep a list of your medicines with you to showyour doctor and pharmacist.

- You should not take methylphenidate hydrochloride tablets on the day of your operation if a certain type of anestheticis used. This isbecause there is a chance of a sudden rise in blood pressure and heart rate during the operation.

Do not start any newmedicine while taking methylphenidate hydrochloride tablets without talking to your doctor first.

How should methylphenidate hydrochloride tablets be taken?

- Take methylphenidate hydrochloride tablets exactly as prescribed. Your doctormay adjust thedose until it is right for you or your child.
- Methylphenidate hydrochloride tablets is usually taken 2 to 3 times a day.
- Take methylphenidate hydrochloride tablets 30 to 45 minutes before a meal.
- From time-to-time, your doctor may stop methylphenidate hydrochloride tablets treatment for a while to checkADHD symptoms.
- Your doctor may do regular checks of the blood, heart, and bloodpressure while takingmethylphenidate hydrochloride tablets.
- Childrenshould have their height and weight checked often whiletakingmethylphenidate hydrochloride tablets. Methylphenidate hydrochloride tablets treatment may be stopped if a problem is found during these check-ups.
- In case of poisoning, call your poisoncontrol center at 1-800-222-1222 right away, or goto the nearest hospitalemergencyroom.

What are the possible side effects of methylphenidate hydrochloride tablets?Methylphenidate hydrochloride tablets may cause serious side effects, including:

- see “What is the most important information I should knowabout methylphenidate hydrochloride tablets?” for information on reported heart and mental problems.
- painful and prolonged erections (priapism) have occurredwith methylphenidate. Ifyou or your child developspriapism, seekmedical help right away. Because of the potential for lasting damage, priapismshould be evaluated by a doctor immediately.
- circulation problems in fingers and toes (peripheral vasculopathy, including Raynaud’s phenomenon):

o fingers or toesmay feel numb, cool, painful

o fingers or toesmay change color from pale, to blue, to red

Tell your doctor if you or your child have, numbness, pain, skin color change, or sensitivityto temperature inthe fingers or toes.

- Call your doctor right away if you have or your child has any signs of unexplained wounds appearing on fingersor toes while taking methylphenidate hydrochloride tablets.
- Slowing of growth (height and weight) in children

Common side effects include:

- fast heart beat
- abnormal heartbeat (palpitations)
- headache
- trouble sleeping
- nervousness
- sweating a lot
- decreased appetite
- dry mouth
- nausea
- stomach pain

Call your doctor for medical advice about side effects.You may report side effects to FDA at1-800-FDA-1088.

How should I store methylphenidate hydrochloride tablets?

- Store methylphenidate hydrochloride tablets in a safe place and in a tightly closed container at room temperature between 68°F to 77°F (20°C to 25°C).
- Protect from light.
- Dispose of remaining, unused, or expired methylphenidate hydrochloride tablets by a medicine take-back program at authorized collection sites, such as retail pharmacies, hospital or clinicpharmacies, and law enforcement locations. If no take-back program or authorizedcollector isavailable, mix methylphenidate hydrochloride tablets with an undesirable, nontoxic substance,such as dirt, cat litter, or used coffee grounds to make it less appealing to children and pets. Place the mixture in a container, such as a sealed plastic bag and throw away (discard) methylphenidate hydrochloride tablets in the household trash.
- Keep methylphenidate hydrochloride tablets and all medicines out of the reach of children.

General information about the safe and effectiveuse ofmethylphenidate hydrochloride tablets.

Medicines are sometimesprescribed for purposes other than those listed in a Medication Guide. You can ask your pharmacist or doctor for information about methylphenidate hydrochloride tablets that is written for healthcareprofessionals. Do not use methylphenidate hydrochloride tablets for a condition for which it was not prescribed. Do not give methylphenidate hydrochloride tablets to other people,even if they have the samesymptoms thatyou have. Itmay harm them and it is against the law.

Whatare theingredientsin methylphenidate hydrochloride tablets?

Active ingredient: Methylphenidate HCl

Inactive ingredients: Colloidal Silicon Dioxide, D&C Yellow #10 Aluminium lake, FD&C Blue #1/Brilliant Blue FCF Aluminium lake (10-mg tablets), Lactose Monohydrate, Magnesium Stearate, Polyethylene glycol, Pregelatinized starch (5-mg and 20-mg tablets), Sucrose.

To report SUSPECTED ADVERSE REACTIONS, contact Ascend Laboratories, LLC at 1-877-ASC-RX01 (877-272-7901) or FDA at 1-800-FDA-1088 or www.fda.gov/medwatch.

Manufactured by:

Alkem Laboratories

1733 Gilsinn Lane, Fenton, MO 63026

Distributed by:

Ascend Laboratories, LLC

Parsippany, NJ 07054

Revised: August, 2021

This Medication Guide has been approved by the U.S. Food and Drug Administration.

L916 (150009) VER 01

PACKAGE LABEL.PRINCIPAL DISPLAY PANEL

NDC 67877-616-01
Methylphenidate Hydrochloride Tablets, USP 5 mg
Rx only
100 Tablets

NDC 67877-616-33
Methylphenidate Hydrochloride Tablets, USP 5 mg
Rx only
10 Tablets

NDC 67877-617-01
Methylphenidate Hydrochloride Tablets, USP 10 mg
Rx only
100 Tablets

NDC 67877-617-33
Methylphenidate Hydrochloride Tablets, USP 10 mg
Rx only
10 Tablets

NDC 67877-618-01
Methylphenidate Hydrochloride Tablets, USP 20 mg
Rx only
100 Tablets

NDC 67877-618-33
Methylphenidate Hydrochloride Tablets, USP 20 mg
Rx only
10 Tablets